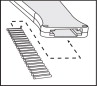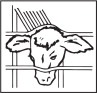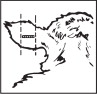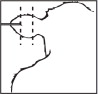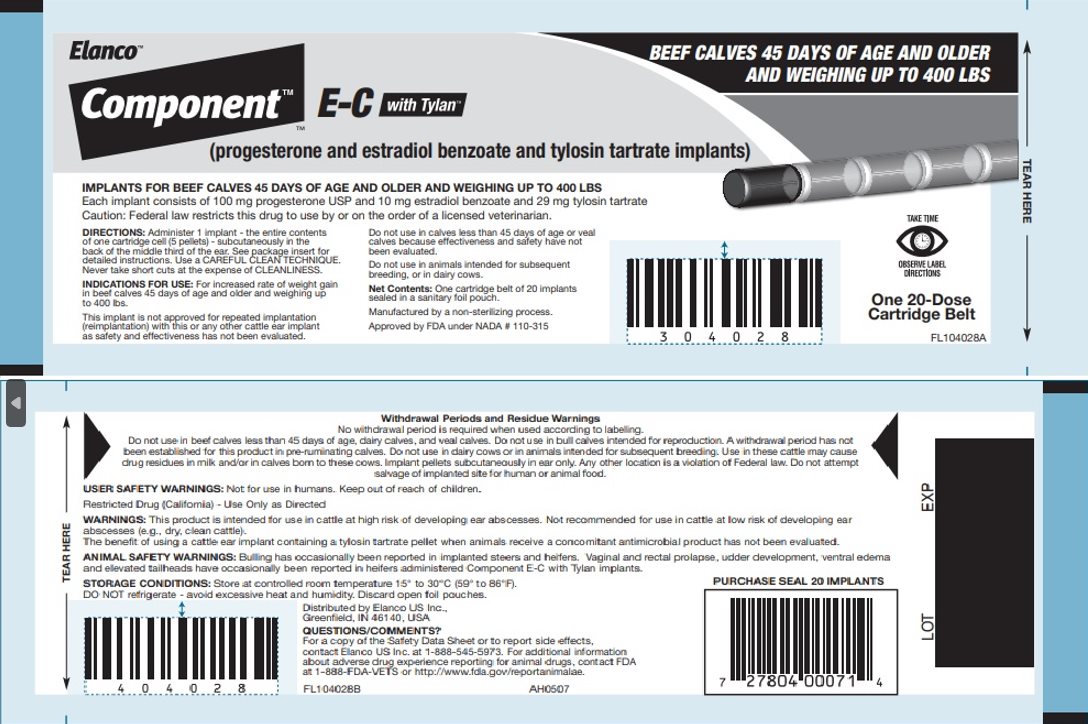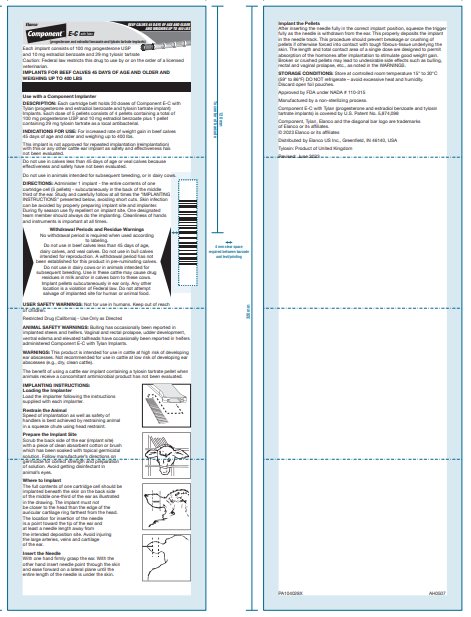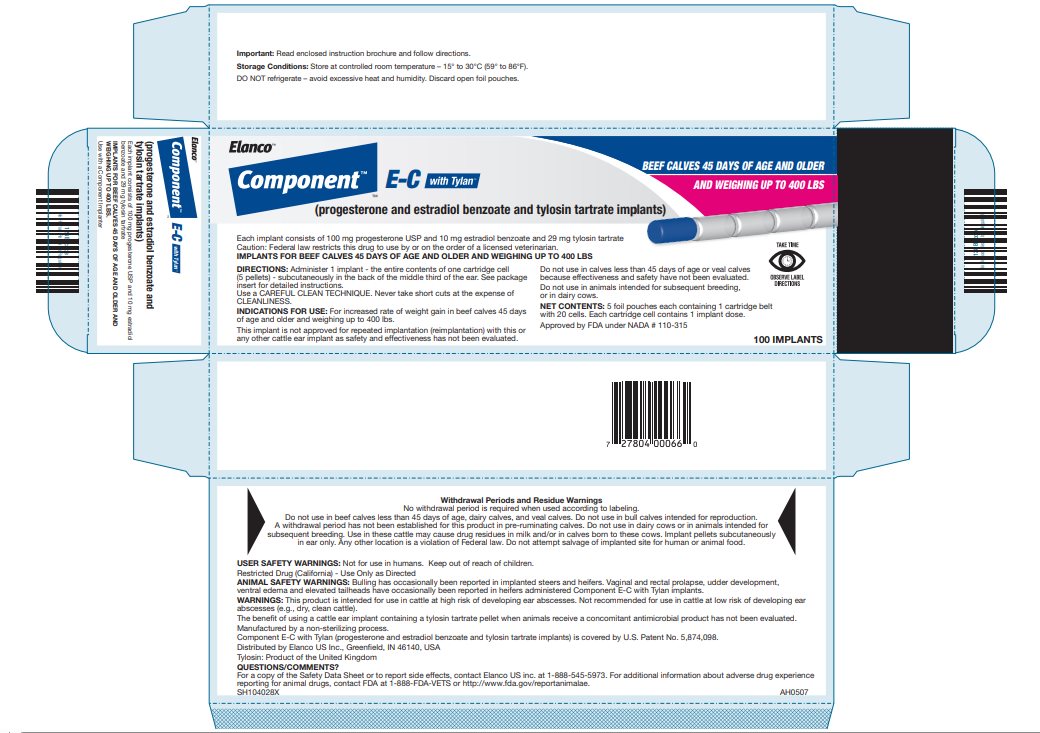 DRUG LABEL: Component E-C With Tylan
NDC: 58198-0507 | Form: IMPLANT
Manufacturer: Elanco US Inc.
Category: animal | Type: PRESCRIPTION ANIMAL DRUG LABEL
Date: 20251121

ACTIVE INGREDIENTS: progesterone 100 mg/1 1; estradiol benzoate 10 mg/1 1; tylosin tartrate 29 mg/1 1

Elanco™

Component™

E-C with Tylan™

(progesterone and estradiol benzoate and tylosin tartrate implant)

BEEF CALVES 45 DAYS OF AGE AND OLDER

AND WEIGHING UP TO 400 LBS

Each implant consists of 100 mg progesterone USP and 10 mg estradiol benzoate and 29 mg tylosin tartrate

Caution: Federal law restricts this drug to use by or on the order of a licensed veterinarian.

IMPLANTS FOR BEEF CALVES 45 DAYS OF AGE AND OLDER AND WEIGHING UP TO 400 LBS

Use with a Component Implanter

DESCRIPTION:

Each cartridge belt holds 20 doses of Component E-C with Tylan (progesterone and estradiol benzoate and tylosin tartrate implant) Implants. Each dose of 5 pellets consists of 4 pellets containing a total of 100 mg progesterone USP and 10 mg estradiol benzoate plus 1 pellet containing 29 mg tylosin tartrate as a local antibacterial.

INDICATIONS FOR USE:

For increased rate of weight gain in beef calves 45 days of age and older and weighing up to 400 lbs.

This implant is not approved for repeated implantation (reimplantation) with this or any other cattle ear implant as safety and effectiveness has not been evaluated.

Do not use in calves less than 45 days of age or veal calves because effectiveness and safety have not been evaluated.

Do not use in animals intended for subsequent breeding, or in dairy cows.

DIRECTIONS:

Administer 1 implant - the entire contents of one cartridge cell (5 pellets) - subcutaneously in the back of the middle third of the ear. Study and carefully follow at all times the "IMPLANTING INSTRUCTIONS" presented below, avoiding short cuts. Skin infection can be avoided by properly preparing implant site and implanter. During fly season use fly repellent on implant site. One designated team member should always do the implanting. Cleanliness of hands and instruments is important at all times.

Withdrawal Periods and Residue Warnings

No withdrawal period is required when used according to labeling.

Do not use in beef calves less than 45 days of age, dairy calves, and veal calves. Do not use in bull calves intended for reproduction. A withdrawal period has not been established for this product in pre-ruminating calves.

Do not use in dairy cows or in animals intended for subsequent breeding. Use in these cattle may cause drug residues in milk and/or in calves born to these cows.

Implant pellets subcutaneously in ear only. Any other location is a violation of Federal law. Do not attempt salvage of implanted site for human or animal food.

USER SAFETY WARNINGS:

Not for use in humans. Keep out of reach of children.

Restricted Drug (California) – Use Only as Directed

ANIMAL SAFETY WARNINGS:

Bulling has occasionally been reported in implanted steers and heifers. Vaginal and rectal prolapse, udder development, ventral edema and elevated tailheads have occasionally been reported in heifers administered Component E-C with Tylan Implants.

WARNINGS:

This product is intended for use in cattle at high risk of developing ear abscesses. Not recommended for use in cattle at low risk of developing ear abscesses (e.g., dry, clean cattle).

The benefit of using a cattle ear implant containing a tylosin tartrate pellet when animals receive a concomitant antimicrobial product has not been evaluated.

IMPLANTING INSTRUCTIONS:

Loading the Implanter

Load the implanter following the instructions supplied with each implanter.

Restrain the Animal

Speed of implantation as well as safety of handlers is best achieved by restraining animal in a squeeze chute using head restraint.

Prepare the Implant Site

Scrub the back side of the ear (implant site) with a piece of clean absorbent cotton or brush which has been soaked with topical germicidal solution. Follow manufacturer's directions on germicide for correct strength and preparation of solution. Avoid getting disinfectant in animal's eyes.

Where to Implant

The full contents of one cartridge cell should be implanted beneath the skin on the back side of the middle one-third of the ear as illustrated in the drawing. The implant must not be closer to the head than the edge of the auricular cartilage ring farthest from the head. The location for insertion of the needle is a point toward the tip of the ear and at least a needle length away from the intended deposition site. Avoid injuring the large arteries, veins and cartilage of the ear.

Insert the Needle

With one hand firmly grasp the ear. With the other hand insert needle point through the skin and ease forward on a lateral plane until the entire length of the needle is under the skin.

Implant the Pellets

After inserting the needle fully in the correct implant position, squeeze the trigger fully as the needle is withdrawn from the ear. This properly deposits the implant in the needle track. This procedure should prevent breakage or crushing of pellets if otherwise forced into contact with tough fibrous-tissue underlying the skin. The length and total contact area of a single dose are designed to permit absorption of the hormones after implantation to stimulate good weight gain. Broken or crushed pellets may lead to undesirable side effects such as bulling, rectal and vaginal prolapse, etc., as noted in the WARNINGS.

STORAGE CONDITIONS:

Store at controlled room temperature 15° to 30°C (59° to 86°F) DO NOT refrigerate – avoid excessive heat and humidity. Discard open foil pouches.

Approved by FDA under NADA # 110-315

Manufactured by a non-sterilizing process.

Component E-C with Tylan (progesterone and estradiol benzoate and tylosin tartrate implants) is covered by U.S. Patent No. 5,874,098

Component, Tylan, Elanco and the diagonal bar logo are trademarks of Elanco or its affiliates.

© 2023 Elanco or its affiliates

Distributed by Elanco US Inc., Greenfield, IN 46140, USA

Tylosin: Product of United Kingdom

Revised: June 2023

PA104028X AH0507

Principal Display Panel - Component E-C With Tylan Cartridge Label

Elanco™

Component™

™

E-C with Tylan™

(progesterone and estradiol benzoate and tylosin tartrate implants)

BEEF CALVES 45 DAYS OF AGE AND OLDER

AND WEIGHING UP TO 400 LBS

Principal Display Panel - Component E-C With Tylan Pouch Label

Elanco™

Component™

™

E-C with Tylan™

(progesterone and estradiol benzoate and tylosin tartrate implant)

BEEF CALVES 45 DAYS OF AGE AND OLDER

AND WEIGHING UP TO 400 LBS

Each implant consists of 100 mg progesterone USP
and 10 mg estradiol benzoate and 29 mg tylosin tartrate

Caution: Federal law restricts this drug to use by or on the order of a licensed veterinarian.

IMPLANTS FOR BEEF CALVES 45 DAYS OF AGE AND OLDER AND WEIGHING UP TO 400 LBS

Principal Display Panel - Component E-C With Tylan Carton Label

Elanco™

Component™

™

E-C with Tylan™

(progesterone and estradiol benzoate and tylosin tartrate implants)

BEEF CALVES 45 DAYS OF AGE AND OLDER

AND WEIGHING UP TO 400 LBS